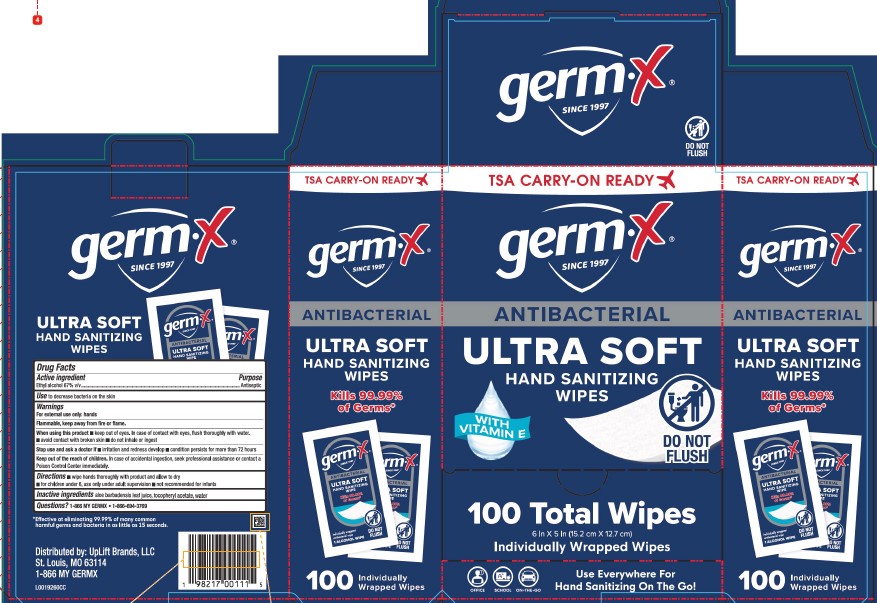 DRUG LABEL: Hand Sanitizing Wipes
NDC: 83986-100 | Form: CLOTH
Manufacturer: UpLift Brands, LLC
Category: otc | Type: HUMAN OTC DRUG LABEL
Date: 20250826

ACTIVE INGREDIENTS: ALCOHOL 67 mL/100 mL
INACTIVE INGREDIENTS: ALOE VERA LEAF; TOCOPHEROL; WATER

Germ-X 100.001/100AA
Hand Sanitizing Wipes

Claims

germ-x®

SINCE 1997

ULTRA SOFT

Hand Sanitizing Wipes

Active ingredient

Ethyl Alcohol 67% v/v

Purpose

Antiseptic

Use

to decrease bacteria on the skin

Warnings

For external use only: hands

Flammable, keep away from fire or flame.

When using this product

- keep out of eyes. In case of contact with eyes, flush thoroughly with water.
- avoid contact with broken skin
- do not inhale or ingest

Stop use and ask a doctor if

- irritation and redness develop
- condition persists for more than 72 hours

Keep out of reach of children.

In case of accidental ingestion, seek professional assistance or contact a Poison Control Center immediately.

Directions

- wipe hands thoroughly with product and allow to dry
- for children under 6, use only under adult supervison
- not recommended for infants

Inactive ingredients

aloe barbadensis leaf juice, tocopheryl acetate, water

Questions?

1-866 MY GERMX 1-866-694-3769

Claims

*Effective at eliminating 99.99% of many common harmful germs and bacteria in as little as 15 seconds.

Side panel claims

TSA CARRY-ON READY

germ-X®

SINCE 1997

ANTIBACTERIAL

Hand Sanitizing Wipes

KILLS 99.99% OF GERMS*

100 INDIVIDUALLY WRAPPED WIPES

Adverse reaction

Distributed by: UpLift Brands, LLC

St. Louis MO 63114

1-866 MY GERMX

Principal display panel

TSA CARRY-ON READY

germ-X®

Since 1997

Antibacterial

Ultra Soft

Hand Sanitizing Wipes

With Vitamin E

DO NOT FLUSH

100 Total Wipes

6 in x 5 in (15.2 cm x 12.7 cm)

Individually Wrapped Wipes

Office · School · On-The-Go

USE EVERYWHERE FOR HAND SANITIZING ON THE GO!